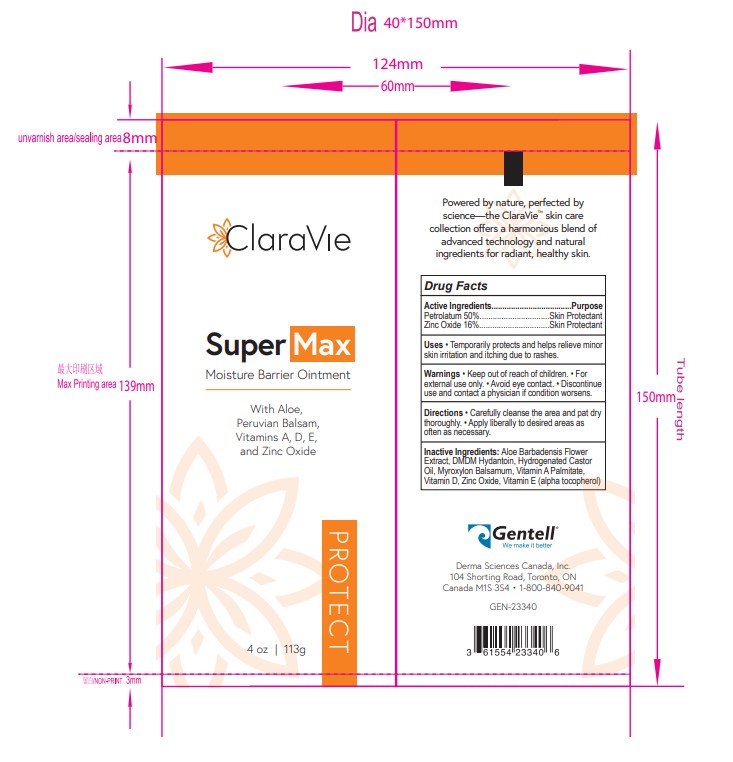 DRUG LABEL: Super Max Barrier Cream
NDC: 61554-700 | Form: CREAM
Manufacturer: Gentell LLC
Category: otc | Type: HUMAN OTC DRUG LABEL
Date: 20241008

ACTIVE INGREDIENTS: ZINC OXIDE 16 g/100 g; PETROLATUM 50 g/100 g
INACTIVE INGREDIENTS: VITAMIN E POLYETHYLENE GLYCOL SUCCINATE; LIGHT MINERAL OIL 16 g/100 g; CASTOR OIL 16 g/100 g; DMDM HYDANTOIN 0.2 g/100 g; ALOE VERA LEAF POLYSACCHARIDES 0.1 g/100 g; CHOLECALCIFEROL 0.4 g/100 g; BALSAM PERU 1 g/100 g; VITAMIN A PALMITATE 0.3 g/100 g

Super Max Moisture Barrier Ointment

Indications & Usage

SuperMax Moisture Barrier Cream protects healthy and intact skin from breaking down during compromised skin conditions.

Directions: Clean the affected area, and dry thoroughly. Apply SuperMax liberally and as often as necessary, especially when prolonged exposure to moisture is anticipated.

Warnings and precautions

Keep out of reach of children

Purpose

Gentell SuperMax Moisture Barrier Cream protects healthy and intact skin from breaking down during compromised skin conditions.

Active Ingredient

Petrolatum

Zinc Oxide

Dosage & administration

Clean the affected area, and dry thoroughly. Apply SuperMax liberally and as often as necessary, especially whenprolonged exposure to moisture is anticipated.

Warnings

For external use only

Avoid all contact with eyes

If condition fails to improve after seven days, consult a physiian

Keep out of reach of children

If swallowed, seek medical attention or call a Poison Control Center immediately

inactive ingredients

Mineral Oil

Castor oil

DMDM Hydantoin

Aloe Vera

Vitamin A Palmitate

vitamin D

Peruvian Balsam

Indication & Usage

Gentell SuperMax Moisture Barrier Cream protects healthy and intact skin from breaking down during compromised skin conditions